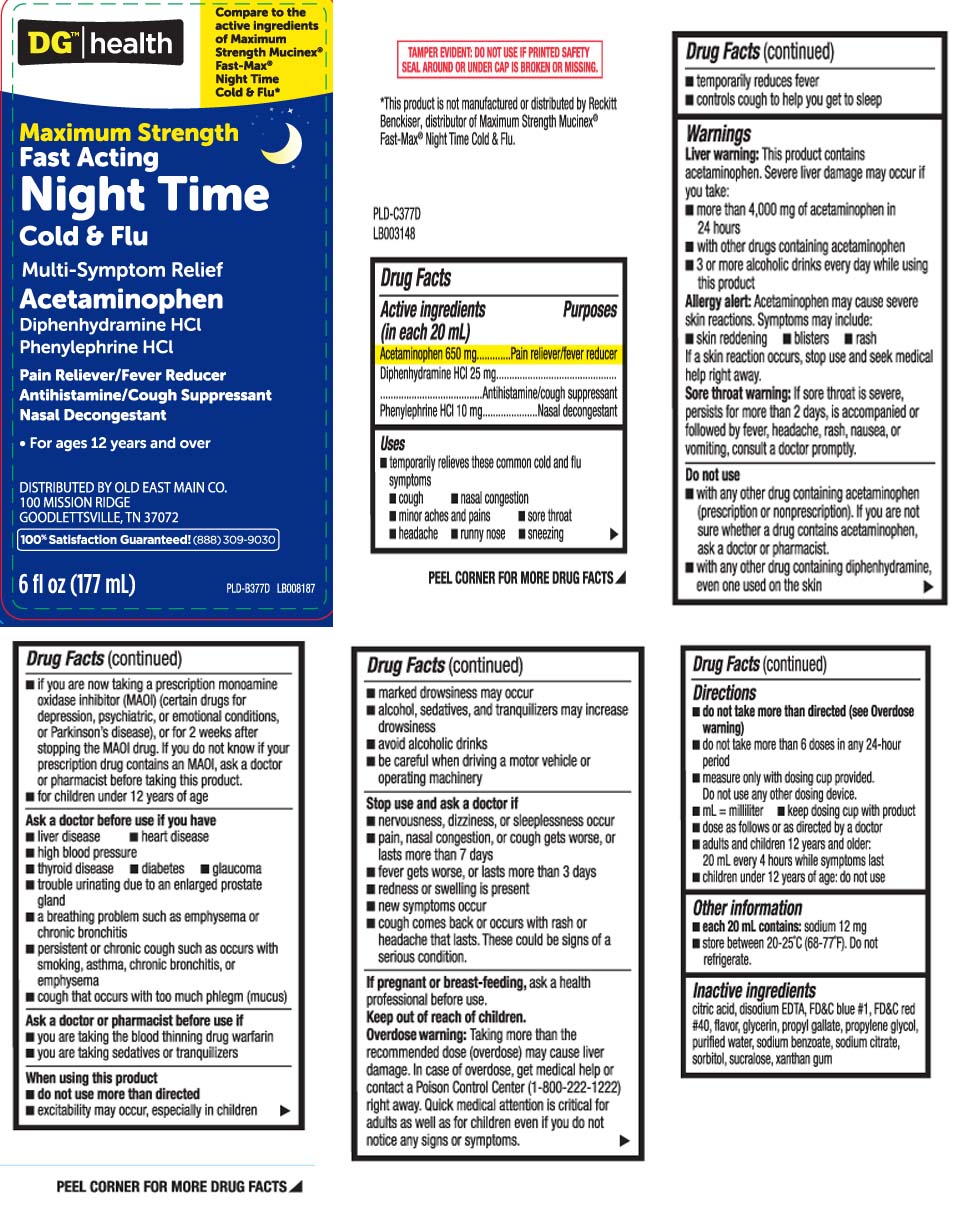 DRUG LABEL: Nighttime Cold and Flu
NDC: 55910-460 | Form: LIQUID
Manufacturer: Dolgencorp, Inc.  (DOLLAR GENERAL & REXALL)
Category: otc | Type: HUMAN OTC DRUG LABEL
Date: 20250708

ACTIVE INGREDIENTS: ACETAMINOPHEN 650 mg/20 mL; DIPHENHYDRAMINE HYDROCHLORIDE 25 mg/20 mL; PHENYLEPHRINE HYDROCHLORIDE 10 mg/20 mL
INACTIVE INGREDIENTS: FD&C BLUE NO. 1; GLYCERIN; PROPYLENE GLYCOL; WATER; SORBITOL; ANHYDROUS CITRIC ACID; FD&C RED NO. 40; PROPYL GALLATE; SODIUM BENZOATE; SODIUM CITRATE; SUCRALOSE; XANTHAN GUM; EDETATE CALCIUM DISODIUM

Drug Facts

Active ingredients (in each 20 mL)

Acetaminophen 650 mg

Diphenhydramine HCI 25 mg

Phenylephrine HCI 10 mg

Purpose

Pain reliever/fever reducer

Antihistamine / cough suppressant

Nasal decongestant

Uses

- temporarily relieves these common cold and flu symptoms
  - cough
  - nasal congestion
  - minor ache and pains
  - sore throat
  - headache
  - runny nose
  - sneezing
- temporarily reduces fever
- controls cough to help you get to sleep

Warnings

Liver warning: This product contains acetaminophen. Severe liver damage may occur if you take:

- more than 4,000 mg of acetaminophen in 24 hours
- with other drugs containing acetaminophen
- 3 or more alcoholic drinks every day while using this product

Allergy alert: Acetaminophen may cause severe skin reactions. Symptoms may include:

- skin reddening
- blisters
- rash

If a skin reaction occurs, stop use and seek medical help right away.

Sore throat warning: If sore throat is severe, persists for more than 2 days, is accompanied or followed by fever, headache, rash, nausea, or vomiting, consult a doctor promptly.

Do not use

- with any other drug containing acetaminophen (prescription or nonprescription). If you are not sure whether a drug contains acetaminophen, ask a doctor or pharmacist.
- with any other drug containing diphenhydramine even one used on the skin
- if you are now taking a prescription monoamine oxidase inhibitor (MAOI) (certain drugs for depression, psychiatric or emotional conditions, or Parkinson’s disease), or for 2 weeks after stopping the MAOI drug. If you do not know if your prescription drug contains an MAOI, ask a doctor or pharmacist before taking this product.
- for children under 12 years of age

Ask a doctor before use if you have

- liver disease
- heart disease
- high blood pressure
- thyroid disease
- diabetes
- glaucoma
- trouble urinating due to an enlarged prostate gland
- a breathing problem such as emphysema or chronic bronchitis
- persistent or chronic cough such as occurs with smoking, asthma, chronic bronchitis or emphysema
- cough that occurs with too much phlegm (mucus)

Ask a doctor or pharmacist before use if you are

- you are taking the blood thinning drug warfarin
- you are taking sedatives or tranquilizers

When using this product

- do not use more than directed
- excitability may occur, especially in children
- avoid alcoholic drinks
- marked drowsiness may occur
- alcohol, sedatives, and tranquilizers may increase drowsiness
- be careful when driving a motor vehicle or operating machinery

Stop use and ask a doctor if

- nervousness, dizziness, or sleeplessness occur
- pain, nasal congestion, or cough gets worse or lasts more than 7 days
- fever gets worse or lasts more than 3 days
- redness or swelling is present
- new symptoms occur
- cough comes back or occurs with rash, or headache that lasts These could be signs of a serious condition.

If pregnant or breast-feeding,

ask a health professional before use.

Keep out of reach of children.

Overdose warning: Taking more than the recommended dose (overdose) can cause liver damage. In case of overdose, get medical help or contact a Poison Control Center (1-800-222-1222) right away. Quick medical attention is critical for adults as well as for children even if you do not notice any signs or symptoms.

Directions

- do not take more than directed (see Overdose warning)
- do not take more than 6 doses in any 24 hours period
- measure only with dosing cup provided. Do not use any other dosing device
- keep dosing cup with product
- mL = milliliter
- dose as follows or as directed by a doctor
- adults and children 12 years and older :
  - 20 mL every 4 hours while symptoms last
- children under 12 years of age do not use

Other information

- each 20 mL contains: sodium 12 mg
- store between 20-25ºC (68-77F). Do not refrigerate

Inactive ingredients

citric acid, disodium EDTA, FD&C blue #1, FD&C red #40, flavor, glycerin, propyl gallate, propylene glycol, purified water sodium benzoate, sodium citrate, sorbitol, sucralose, xanthan gum

Principal Display Panel

Compare to the active ingredients of Maximum Strength Mucinex® Fast-Max® Night Time Cold & Flu*

Maximum Strength

Fast Acting

Night Time Cold & Flu

Multi-Symptom Relief

Acetaminophen

Diphenhydramine HCI

Phenylephrine HCI

Pain Reliever/Fever Reducer

Antihistamine/Cough Suppressant

Nasal Decongestant

- For ages 12 years and over

FL OZ (mL)

*This product is not manufactured or distributed by Reckitt Benckiser, distributor of Maximum Strength Mucinex® Fast-Max® Night Time Cold & Flu

TAMPER EVIDENT: DO NOT USE IF PRINTED SAFETY SEAL AROUND OR UNDER CAP IS BROKEN OR MISSING.

DISTRIBUTED BY OLD EAST MAIN CO.

100 MISSION RIDGE

GOODLETTSVILLE, TN 37072

Product Label

DOLLAR GENERAL HEALTH Mucus Relief Night Time Cold and Flu